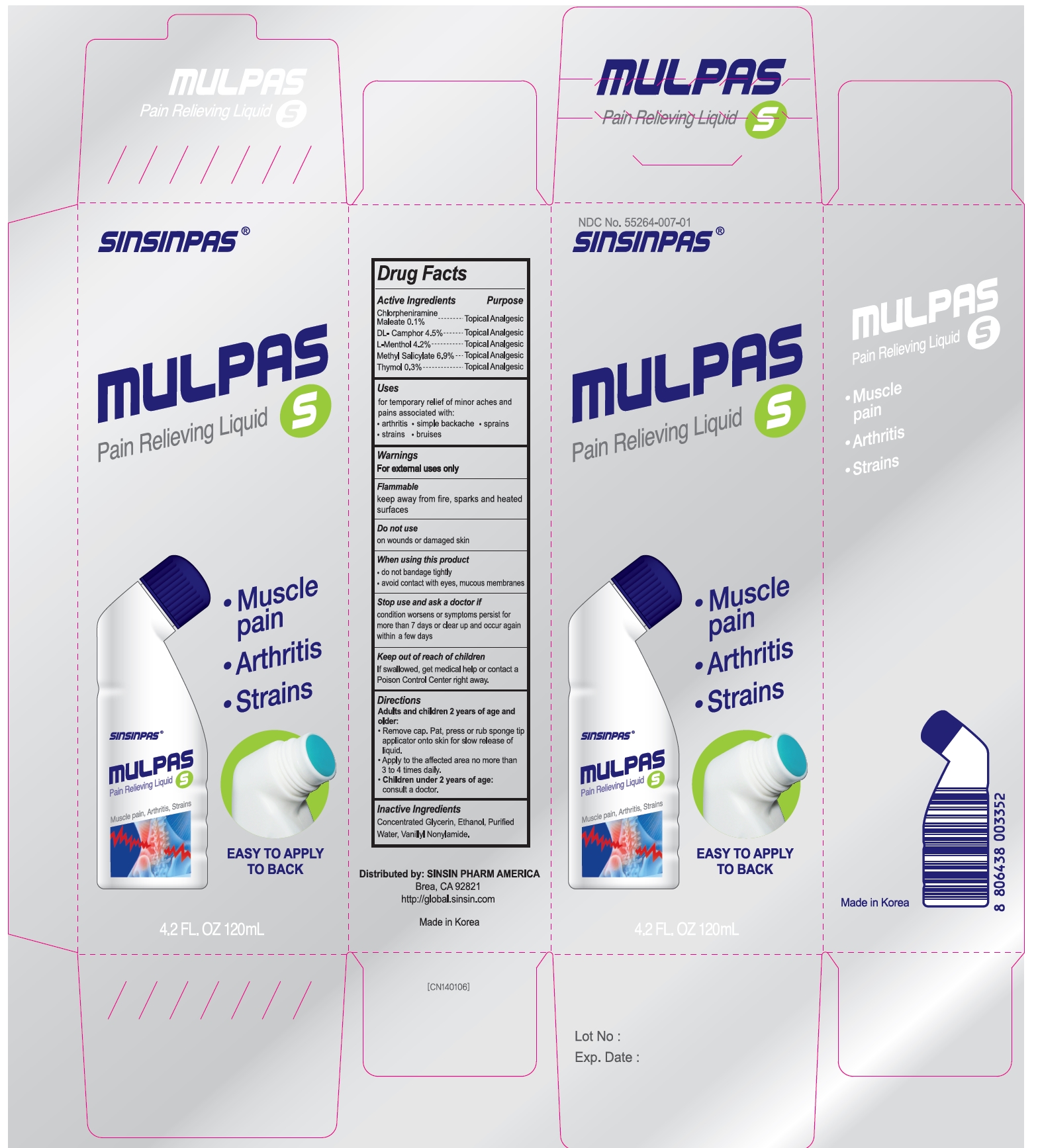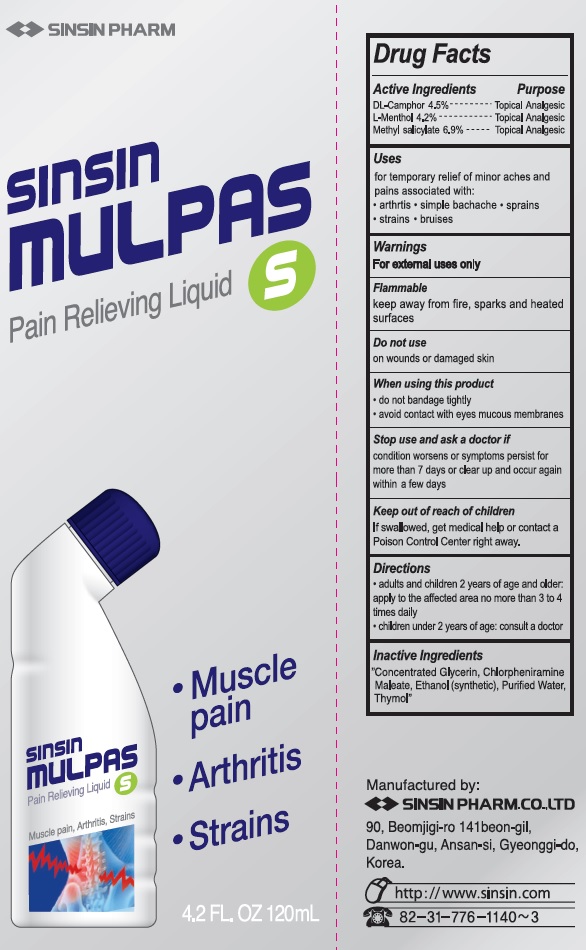 DRUG LABEL: Sinsin Mulpas
NDC: 55264-007 | Form: LIQUID
Manufacturer: Sinsin Pharmaceutical Co., Ltd.
Category: otc | Type: HUMAN OTC DRUG LABEL
Date: 20250107

ACTIVE INGREDIENTS: CAMPHOR (SYNTHETIC) 4.5 mg/1 mL; LEVOMENTHOL 4.2 mg/1 mL; METHYL SALICYLATE 6.9 mg/1 mL
INACTIVE INGREDIENTS: GLYCERIN; CHLORPHENIRAMINE MALEATE; ALCOHOL; WATER; THYMOL

SINSIN MULPAS

Active ingredients

DL-Camphor 4.5%

L-Menthol 4.2%

Methyl Salicylate 6.9%

Purpose

Topical Analgesic

Uses

for temporary relief of minor aches and pains of muscles and joints associated with:

- arthritis
- simple backache
- strains
- bruises
- sprains

For external use only.

Flammable

keep away from fire, sparks and heated surfaces

Do not use

- on wounds or damaged skin

When using this product

- do not bandage tightly
- avoid contact with the eyes mucous membranes

Stop use and ask a doctor if

condition worsens or symptoms persist for more than 7 days or clear up and occur again within a few days

Keep out of reach of children.

If swallowed, get medical help or contact a Poison Control Center right away.

Directions

Adults and children 12 years of age and over:

- adults and children 2 years of age and older: apply to the affected area no more than 3 to 4 times daily.
- children under 2 years of age: consult a doctor

Children under 12 years of age:

- Consult a doctor.

Inactive ingredients

Concentrated Glycerin, Chlorpheniramine Maleate, Ethanol (synthetic), Purified Water, Thymol

Manufactured by:

SINSIN PHARM. CO., LTD.

90, Beomjigi-ro 141 beon-gil, Danwon-Gu, Ansan-si, Gyeonggi-do, Korea

http://www.sinsin.com tel: 82-31-776-1140~3